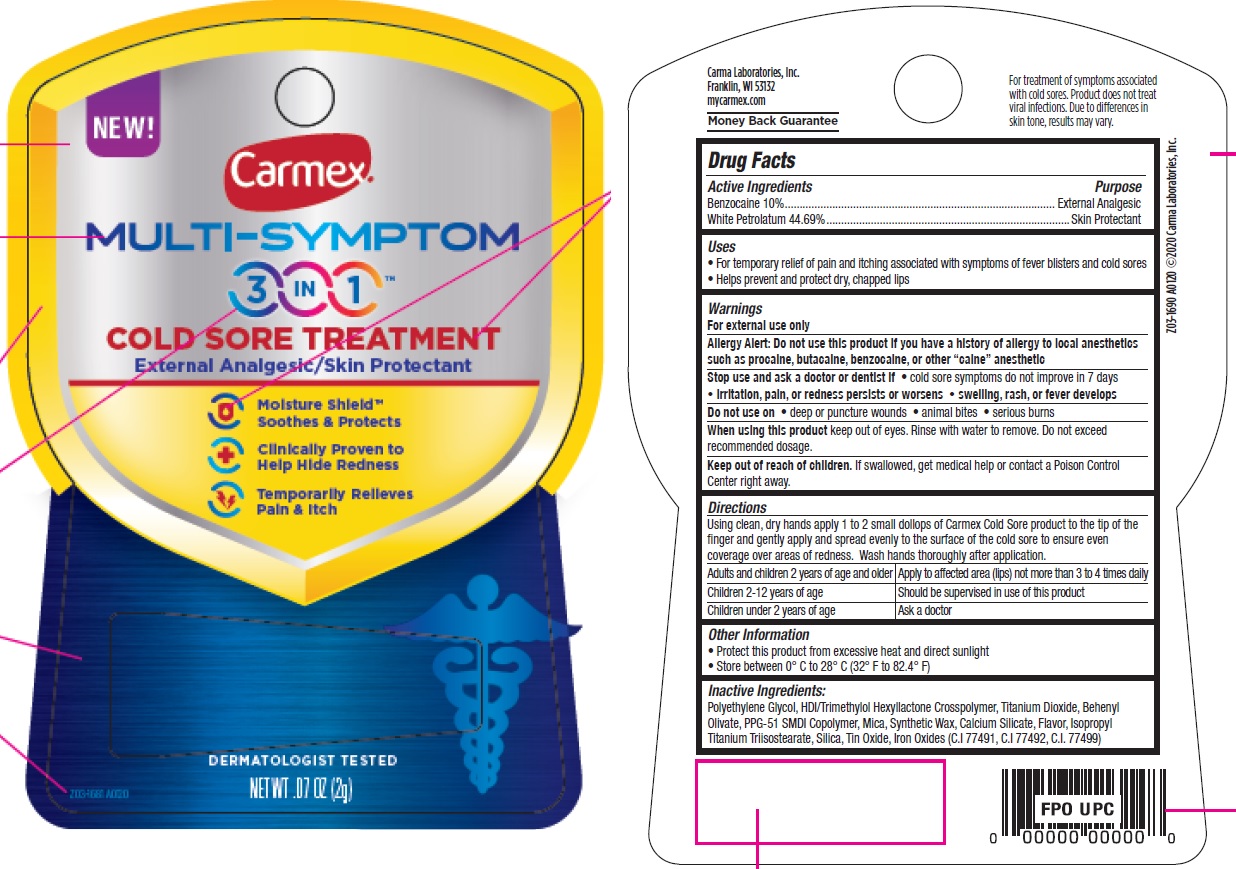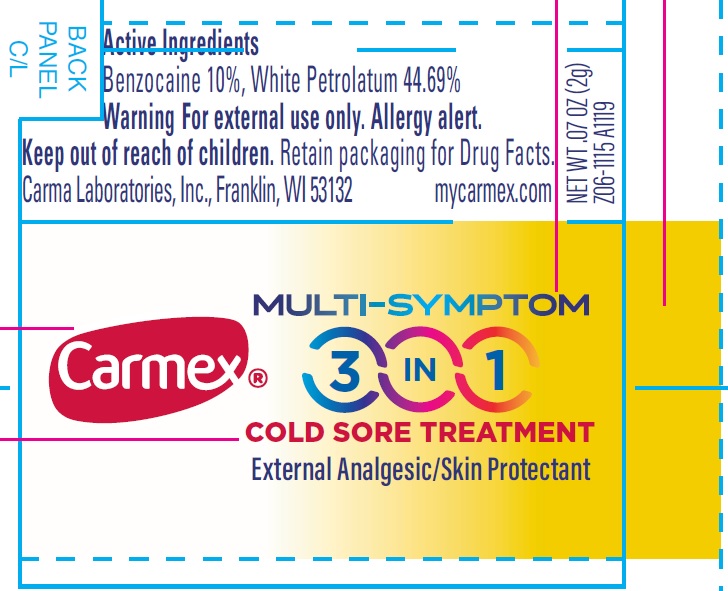 DRUG LABEL: CARMEX Multi-Symptom 3 in 1 COLD Sore treatment External Analgesic Skin Protectant
NDC: 10210-0048 | Form: CREAM
Manufacturer: Carma Laboratories, Inc.
Category: otc | Type: HUMAN OTC DRUG LABEL
Date: 20231025

ACTIVE INGREDIENTS: BENZOCAINE 100 mg/1 g; WHITE PETROLATUM 446.9 mg/1 g
INACTIVE INGREDIENTS: POLYETHYLENE GLYCOL, UNSPECIFIED; HEXAMETHYLENE DIISOCYANATE/TRIMETHYLOL HEXYLLACTONE CROSSPOLYMER; TITANIUM DIOXIDE; BEHENYL OLIVATE; PPG-51/SMDI COPOLYMER; MICA; CALCIUM SILICATE; ISOPROPYL TITANIUM TRIISOSTEARATE; SILICON DIOXIDE; STANNIC OXIDE; FERRIC OXIDE RED; FERRIC OXIDE YELLOW; FERROSOFERRIC OXIDE

CARMEX Multi-Symptom 3 in 1 COLD Sore treatment External Analgesic Skin Protectant

Active Ingredients

Benzocaine 10%

White Petrolatum 44.69%

Purpose

External Analgesic

Skin Protectant

Uses

• For temporary relief of pain and itching associated with symptoms of fever blisters and cold sores • Helps prevent and protect dry, chapped lips

Warnings

For external use only

Allergy Alert: Do not use this product if you have a history of allergy to local anesthetics such as procaine, butacaine, benzocaine, or other “caine” anesthetic

Stop use and ask a doctor or dentist if

• cold sore symptoms do not improve in 7 days

• irritation, pain, or redness persists or worsens • swelling, rash, or fever develops

Do not use on

• deep or puncture wounds • animal bites • serious burns

When using this product

keep out of eyes. Rinse with water to remove. Do not exceed recommended dosage.

Keep out of reach of children.

If swallowed, get medical help or contact a Poison Control Center right away.

Directions

Using clean, dry hands apply 1 to 2 small dollops of Carmex Cold Sore product to the tip of the finger and gently apply and spread evenly to the surface of the cold sore to ensure even coverage over areas of redness. Wash hands thoroughly after application.

Adults and children 2 years of age and older | Apply to affected area (lips) not more than 3 to 4 times daily
Children 2-12 years of age | Should be supervised in use of this product
Children under 2 years of age | Ask a doctor

Other Information

• Protect this product from excessive heat and direct sunlight • Store between 0° C to 28° C (32° F to 82.4° F)

Inactive Ingredients:

Polyethylene Glycol, HDI/Trimethylol Hexyllactone Crosspolymer, Titanium Dioxide, Behenyl Olivate, PPG-51 SMDI Copolymer, Mica, Synthetic Wax, Calcium Silicate, Flavor, Isopropyl Titanium Triisostearate, Silica, Tin Oxide, Iron Oxides (C.I 77491, C.I 77492, C.I. 77499)